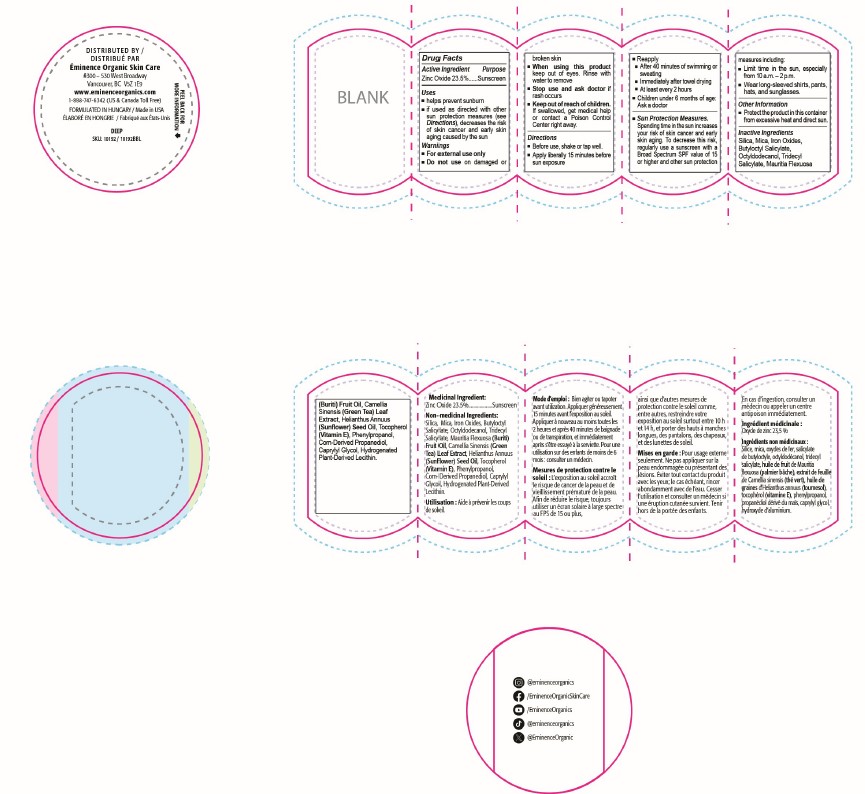 DRUG LABEL: Sun Defense Minerals (Deep)
NDC: 15751-3605 | Form: POWDER
Manufacturer: Eminence Organic Skin Care
Category: otc | Type: HUMAN OTC DRUG LABEL
Date: 20250301

ACTIVE INGREDIENTS: ZINC OXIDE 235 mg/1 g
INACTIVE INGREDIENTS: PHENYLPROPANOL; PROPANEDIOL; MAURITIA FLEXUOSA FRUIT OIL; BUTYLOCTYL SALICYLATE; IRON OXIDES; TRIDECYL SALICYLATE; CAPRYLYL GLYCOL; HYDROGENATED SOYBEAN LECITHIN; OCTYLDODECANOL; TOCOPHEROL; MICA; HELIANTHUS ANNUUS (SUNFLOWER) SEED OIL; CAMELLIA SINENSIS LEAF; HYDRATED SILICA

Sun Defense Minerals (Deep) Pro

Directions

Before use, shake or tap well
Apply liberally 15 minutes before sun exposure
Reapply

After 40 minutes of swimming or sweating
Immediately after towel drying
At least every 2 hours

Children under 6 months of age: Ask a doctor

Sun Protection Measures.

Spending time in the sun increases your risk of skin cancer and early skin aging. To decrease this risk, regularly use a sunscreen with a Broad Spectrum SPF value of 15 or higher and other sun protection measures including:

Limit time in the sun, especially from 10 a.m. – 2 p.m.
Wear long-sleeved shirts, pants, hats, and sunglasses.

Warnings

For external use only
Do not use on damaged or broken skin

When using this product keep out of eyes. Rinse with water to remove
Stop use and ask a doctor if rash occurs

Keep out of reach of children. If swallowed, get medical help or contact a Poison Control Center right away.

Inactive ingredients

Silica, Mica, Butyloctyl Salicylate, Octyldodecanol, Tridecyl Salicylate, Iron Oxides, Mauritia Flexuosa (Buriti) Fruit Oil, Camellia Sinensis (Green Tea) Leaf Extract, Helianthus Annuus (Sunflower) Seed Oil, Tocopherol (Vitamin E), Phenylpropanol, Corn-Derived Propanediol, Caprylyl Glycol, Hydrogenated Plant-Derived Lecithin.

Uses

helps prevent sunburn

if used as directed with other sun protection measures (see Directions), decreases the risk of skin cancer and early skin aging caused by the sun

Keep out of reach of children. If swallowed, get medical help or contact a Poison Control Center right away.

Active Ingredient Purpose

Zinc Oxide 23.5%......Sunscreen

Purpose: Sunscreen

Drug Facts

Active Ingredient Purpose

Zinc Oxide 23.5%......Sunscreen

Uses

helps prevent sunburn

if used as directed with other sun protection measures (see Directions), decreases the risk of skin cancer and early skin aging caused by the sun

Warnings

Do not use on damaged or broken skin

When using this product keep out of eyes. Rinse with water to remove

Stop use and ask a doctor if rash occurs

Keep out of reach of children. If swallowed, get medical help or contact a Poison Control Center right away.

Directions

Before use, shake or tap well

Apply liberally 15 minutes before sun exposure

Reapply

After 40 minutes of swimming or sweating

Immediately after towel drying

At least every 2 hours

Children under 6 months of age: Ask a doctor

Sun Protection Measures.

Spending time in the sun increases your risk of skin cancer and early skin aging. To decrease this risk, regularly use a sunscreen with a Broad Spectrum SPF value of 15 or higher and other sun protection measures including:

Limit time in the sun, especially from 10 a.m. – 2 p.m.
Wear long-sleeved shirts, pants, hats, and sunglasses.

Other information

Protect the product in this container from excessive heat and direct sun

Inactive ingredients

Silica, Mica, Butyloctyl Salicylate, Octyldodecanol, Tridecyl Salicylate, Iron Oxides, Mauritia Flexuosa (Buriti) Fruit Oil, Camellia Sinensis (Green Tea) Leaf Extract, Helianthus Annuus (Sunflower) Seed Oil, Tocopherol (Vitamin E), Phenylpropanol, Corn-Derived Propanediol, Caprylyl Glycol, Hydrogenated Plant-Derived Lecithin.